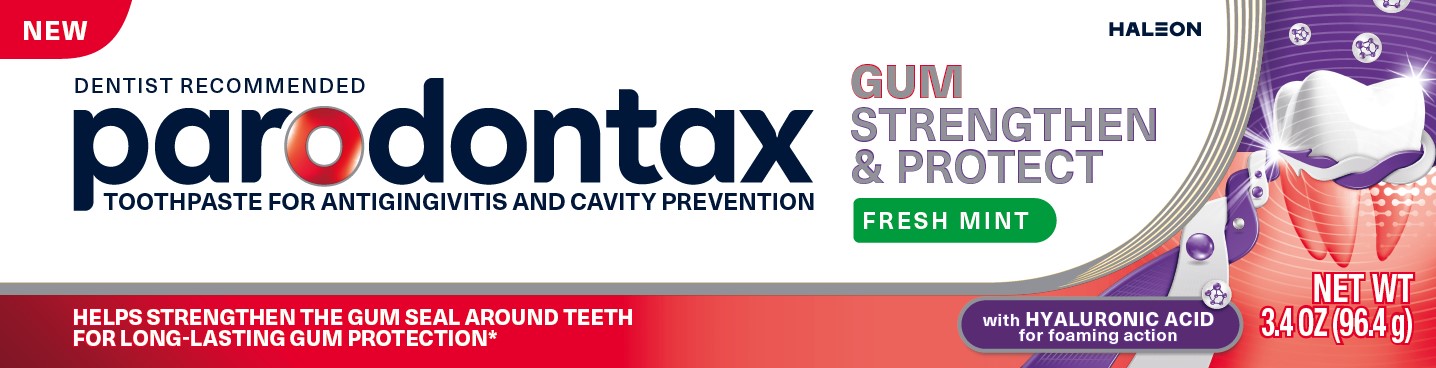 DRUG LABEL: Parodontax

NDC: 0135-0655 | Form: PASTE, DENTIFRICE
Manufacturer: Haleon US Holdings LLC
Category: otc | Type: HUMAN OTC DRUG LABEL
Date: 20251215

ACTIVE INGREDIENTS: STANNOUS FLUORIDE 1.5 mg/1 g
INACTIVE INGREDIENTS: GLYCERIN; POLYETHYLENE GLYCOL 400; HYDRATED SILICA; SODIUM TRIPOLYPHOSPHATE ANHYDROUS; SODIUM LAURYL SULFATE; POLYACRYLIC ACID (250000 MW); COCAMIDOPROPYL BETAINE; SACCHARIN SODIUM; HYALURONATE SODIUM; BASIC BLUE 1

Drug Facts

Active ingredient

Stannous fluoride 0.454% (0.15% w/v fluoride ion)

Purpose

Anticavity, Antigingivitis

Uses

- aids in the prevention of dental cavities.
- helps control bleeding gums.
- helps interfere with harmful effects of plaque associated with gingivitis.

Warnings

Stop use and ask a dentist if

- gingivitis, bleeding, or redness persists for more than 2 weeks.
- you have painful or swollen gums, pus from the gum line, loose teeth, or increasing spacing between the teeth. These may be signs or symptoms of periodontitis, a serious form of gum disease

Keep out of reach of children under 6 years of age.

If more than used for brushing is accidentally swallowed, get medical help or contact a Poison Control Center right away.

Directions

- adults and children 2 years of age and older:
  - brush teeth thoroughly, preferably after each meal or at least twice a day, or as directed by a dentist or doctor. Minimize swallowing.
  - to minimize swallowing for children under 6 years of age, use a pea-sized amount and supervise brushing and rinsing until good habits are established.
- children under 2 years of age:Consult a dentist or doctor.

Other information

- products containing stannous fluoride may produce surface staining of the teeth. Adequate toothbrushing may prevent these stains which are not harmful or permanent and may be removed by your dentist.
- this product is specially formulated to help prevent staining.
- do not store above 25°C (77°F)

Inactive ingredients

glycerin, PEG-8, hydrated silica, pentasodium triphosphate, flavor, sodium lauryl sulfate, polyacrylic acid, cocamidopropyl betaine, sodium saccharin, sodium hyaluronate, blue 1

Questions or comments?

1-866-844-2797

Additional Information

ALWAYS FOLLOW THE LABEL

parodontax

GUM STRENGTHEN & PROTECT

Healthy gums form a tight seal around teeth. Reducing plaque bacteria build-up helps to prevent gum problems.

parodontax Gum Strengthen & Protectdaily fluoride toothpaste helps strengthen the gum seal around teeth for long-lasting gum protection.*

With Hyaluronic Acid,this toothpaste delivers foaming action for an elevated brushing experience.

*with continued twice daily use

1 STRENGTHEN

Kills plaque bacteria along the gumline for a stronger and tighter seal between gums and teeth.

2 PROTECT

Helps prevent plaque bacteria build-up to maintain healthy gums every day.*

Principal Display Panel

NEW

DENTIST RECOMMENDED

parodontax

TOOTHPASTE FOR ANTIGINGIVITIS AND CAVITY PROTECTION

GUM STRENGTHEN & PROTECT

FRESH MINT

HELPS STRENGTHEN THE GUM SEAL AROUND TEETH FOR LONG-LASTING GUM PROTECTION*

with HYALURONIC ACID for foaming action

NET WT 3.4 OZ (96.4 g)